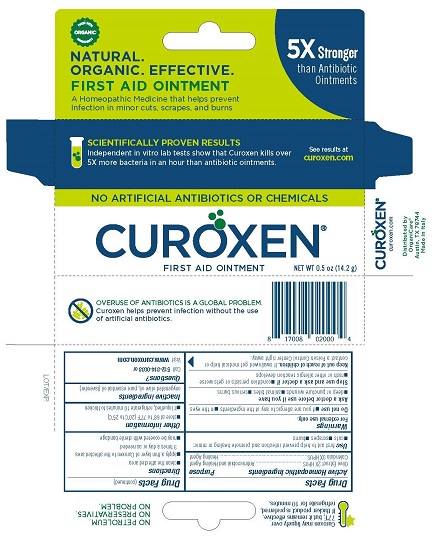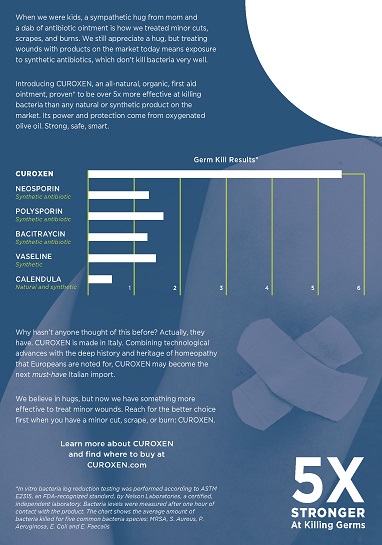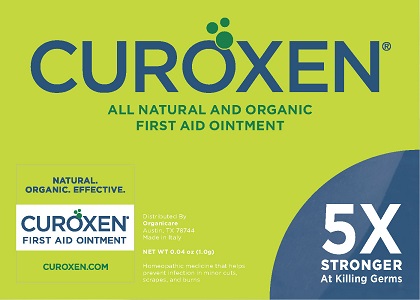 DRUG LABEL: Curoxen
NDC: 71042-001 | Form: OINTMENT
Manufacturer: OrganiCare Nature's Science, LLC
Category: homeopathic | Type: HUMAN OTC DRUG LABEL
Date: 20241212

ACTIVE INGREDIENTS: OLEA EUROPAEA FRUIT VOLATILE OIL 2 [hp_X]/14 g; CALENDULA OFFICINALIS FLOWERING TOP 3 [hp_X]/14 g
INACTIVE INGREDIENTS: LAVENDER OIL; OLIVE OIL

CUROXEN FIRST AID OINTMENT

Drug Facts

Active Homeopathic Ingredients

Olive Extract 2X HPUS

Calendula 3X HPUS

Purpose

Antimicrobial Healing Agent

Healing Agent

Use

first aid to help prevent infection and promote healing in minor:

- cuts
- scrapes
- burns

Warnings

For external use only.

Do not use

- if you are allergic to any of the ingredients
- in the eyes

Ask a doctor before use if you have

- deep or puncture wounds
- animal bites
- serious burns

Stop use and ask a doctor if

- condition persists or gets worse
- rash or other allergic reaction develops

Keep out of reach of children. If swallowed, get medical help or contact a Poison Control Center right away.

Directions

- clean the affected area
- apply a thin layer of Curoxen to the affected area 3 times a day or as needed
- may be covered with a sterile bandage

Other information

- store at 68° to 77°F (20° to 25°C)
- if liquefied, refrigerate 10 minutes to thicken

Inactive ingredients

oxygenated olive oil, pure essential oil (lavender)

Questions?

Call 512-814-0038 or

Visit www.curoxen.com

Distributed by

OrganiCare®

Austin, TX 78744

Made in Italy

When we were kids, a sympathetic hug from mom and a dab of antibiotic ointment is how we treated minor cuts, scrapes, and burns. We still appreciate a hug, but treating wounds with most products on the market today means exposure to synthetic antiobiotics, which don't kill bacteria very well.

Introducing CUROXEN, an all-natural, organic first aid ointment, proven* to be over 5x more effective at killing bacteria than any other natural or synthetic product on the market. Its power and protection come from oxygened olive oil. Strong, safe, smart.

[CHART]

Why hasn't anyone thought of this before? Actually they have. CUROXEN is made in Italy. Combining technological advances with the deep history and heritage of homeopathy that Europeans are noted for, CUROXEN may become the next must-have Italian import.

We believe in hugs, but now we have something more effective to treat minor wounds. Reach for the better choice first when you have a minor cut, scrape, or burn: CUROXEN.

* In vitro bacteria log reduction testing was performed according to ASTM E2315, and FDA-recognized standard, by Nelson Laboratories, a certified, independent laboratory. Bacteria levels were measured after one hour of contact with the product. The chart shows the average amount of bacteria killed for five common bacteria species: MRSA, S. Aureus, P. Aeroginosa, E. Coli and E. Faecalis.

PACKAGE LABEL

CUROXEN®
FIRST AID OINTMENT

A Homeopathic Medicine that helps prevent Infection in minor cuts, scrapes, and burns

NET WT 0.5 oz (14.2 g)

PACKAGE LABEL

CUROXEN®

ALL NATURAL AND ORGANIC FIRST AID OINTMENT

5X STRONGER At Killing Germs

Distributed By:

OrganiCare

Austin, TX 78744

Made in Italy

NET WT 0.04 oz (1.0 g)

Homeopathic medicine that helps prevent infection in minor cuts, scrapes, and burns